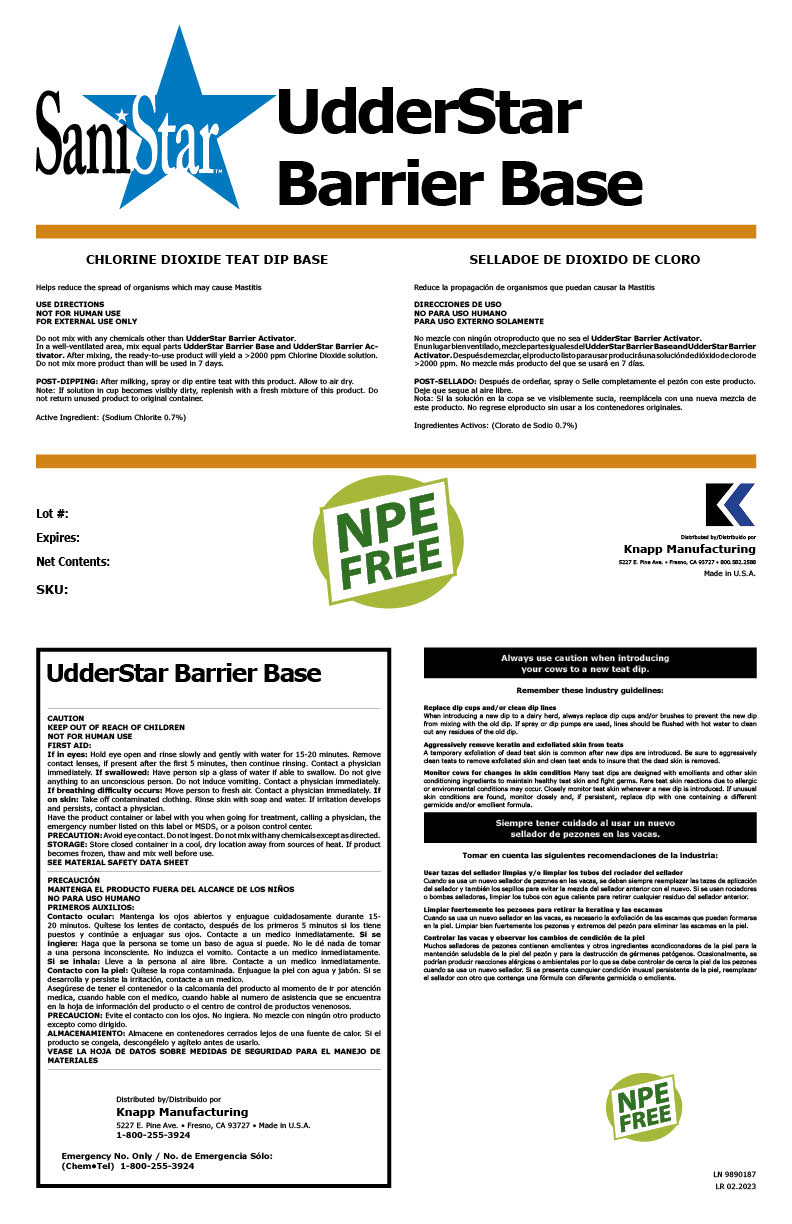 DRUG LABEL: Udderstar Barrier Base
NDC: 43104-2018 | Form: LIQUID
Manufacturer: Knapp Manufacturing, Inc.
Category: animal | Type: OTC ANIMAL DRUG LABEL
Date: 20230221

ACTIVE INGREDIENTS: SODIUM CHLORITE 0.7 g/100 g
INACTIVE INGREDIENTS: WATER

Udderstar Barrier Base

Summary of effectiveness

Helps reduce the spread of organisms which may
cause Mastitis

Instructions for use

POST-DIPPING: After milking, spray or dip entire teat with this product. Allow to air dry.
Note: If solution in cup becomes visibly dirty, replenish with a fresh mixture of this product. Do
not return unused product to original container.

Safe Handling

NOT FOR HUMAN USE
FOR EXTERNAL USE ONLY
Do not mix with any chemicals other than UdderStar Barrier Activator.
In a well-ventilated area, mix equal parts UdderStar Barrier Activator and UdderStar Barrier

General Precautions

CAUTION
KEEP OUT OF REACH OF CHILDREN
NOT FOR HUMAN USE

Avoid eye contact. Do not ingest. Do not mix with any chemicals except as directed.

Storage and Handling

Store closed container in a cool, dry location away from sources of heat. If product
becomes frozen, thaw and mix well before use.